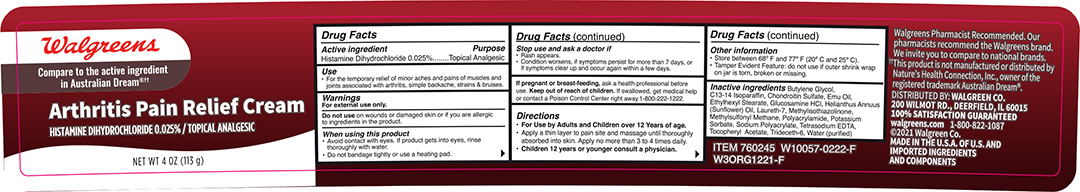 DRUG LABEL: Walgreens Arthritis Pain Relief Cream
NDC: 0363-5301 | Form: CREAM
Manufacturer: Walgreens Company
Category: otc | Type: HUMAN OTC DRUG LABEL
Date: 20241120

ACTIVE INGREDIENTS: HISTAMINE DIHYDROCHLORIDE 0.00025 g/1 g
INACTIVE INGREDIENTS: BUTYLENE GLYCOL; C13-14 ISOPARAFFIN; CHONDROITIN SULFATE (SHARK); EMU OIL; ETHYLHEXYL STEARATE; GLUCOSAMINE HYDROCHLORIDE; HELIANTHUS ANNUUS FLOWERING TOP; LAURETH-7; METHYLISOTHIAZOLINONE; DIMETHYL SULFONE; POLYACRYLAMIDE (1500 MW); POTASSIUM SORBATE; SODIUM POLYACRYLATE (8000 MW); TETRASODIUM EDETATE DIHYDRATE; .ALPHA.-TOCOPHEROL ACETATE; TRIDECETH-6; WATER

Active Ingredient

Histamine Dihydrochloride 0.025%

Purpose

Topical Analgesic

Uses

For temporary relief of minor aches and pains of muscles and joints assited with arthritis, simple backache, strains & bruises.

Warnings

For external use only.

Do not use on wounds or damaged skin or if you are allergic to ingredients in the product.

When using this product

Avoid contact with eyes. If product gets into eyes,rinse thoroughly with water.

Do not bandage tightly or use a heating pad.

Stop use and ask a doctor if

Rash appears.

Condition worsens, if symptoms persist for more than 7 days, or if symptoms clear up and occur again within a few days.

PREGNANCY OR BREAST FEEDING

If pregnant or breast-feeding, ask a health professional before use.

KEEP OUT OF REACH OF CHILDREN

Keep out of the reach of children. If swallowed, get medical help or contact a Poison Control Center right away.

DOSAGE AND ADMINISTRATION

For use by adults and Children over 12 years of age.

apply a thin layer to the pain site and massage until thoroughly absorbed into skin. Apply no more than 3 to 4 times daily.
Children 12 years or younger consult a physician.

Other Information

Store between 68° and 77° F (20° and 25° C)

Tamper evident feature:do not use if outer shrink wrap on jar is torn, broken or missing.

Inactive Ingredients

Butylene Glycol, C13-C14 Isoparaffin, Chondroitin Sulfate, Emu Oil, Ethylhexyl Stearate, Glucosamine HCL, Hellanthus Annuus(Sunflower)Oil, Laureth-7, Methylisothiazolinone, Methylsulfonylmethane,Polyacrylamide, Potassium Sorbate, Sodium Polyacrylate, Tetrasodium EDTA, Tocopheryl Acetate, Trideceth-6, Water (purified)

Principal Display Panel -Jar

Walgreens Arthritis Pain Relief NDC 0363-5301-40

Histamine Dihydrochloride 0.025%

Arthritis Pain Relief Cream

NET WT 4OZ (113g)